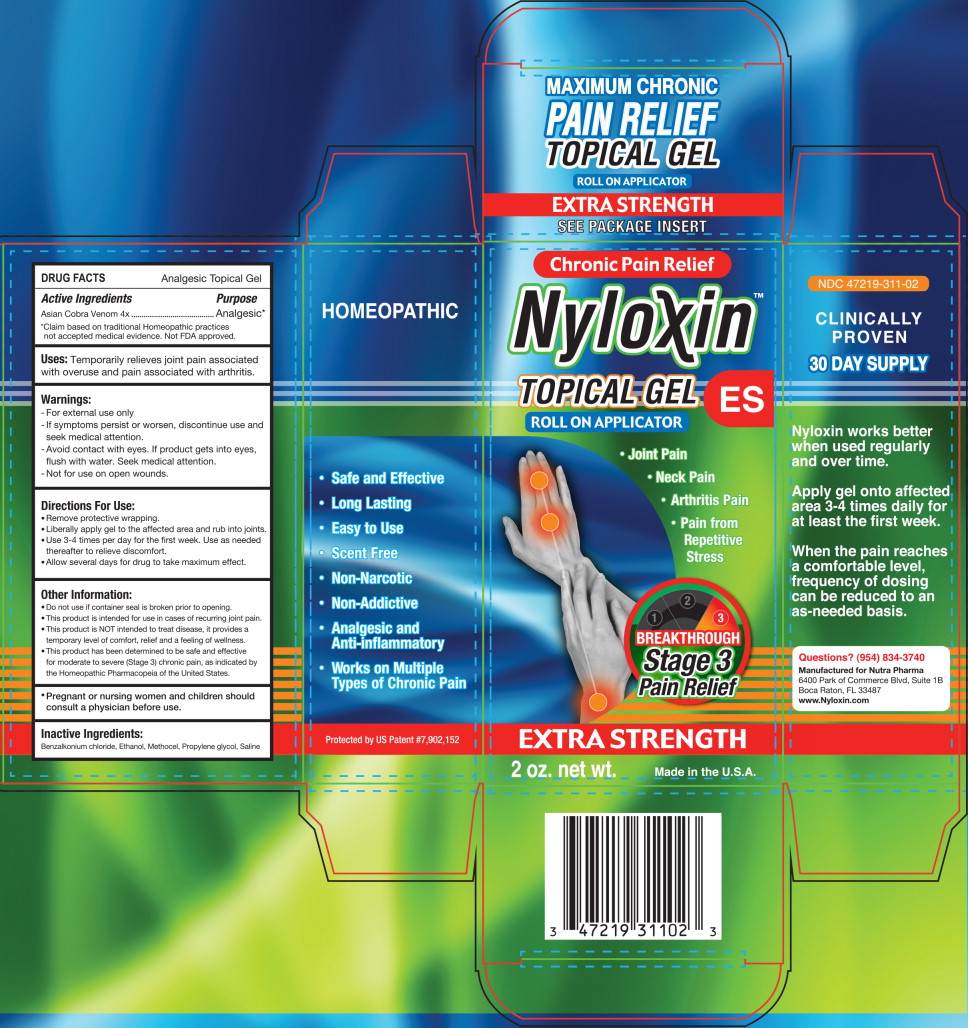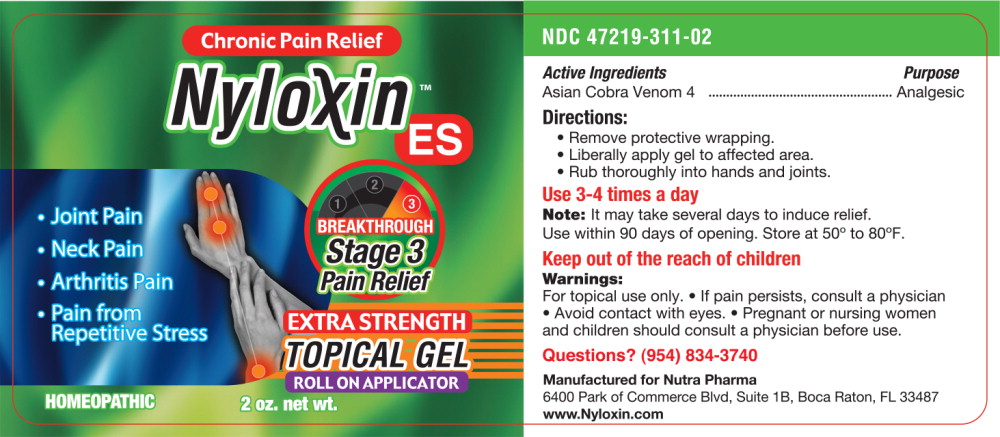 DRUG LABEL: Nyloxin
NDC: 47219-311 | Form: GEL
Manufacturer: Nutra Pharma Corporation
Category: homeopathic | Type: HUMAN OTC DRUG LABEL
Date: 20251020

ACTIVE INGREDIENTS: NAJA NAJA VENOM 4 [hp_X]/1 mL
INACTIVE INGREDIENTS: BENZALKONIUM CHLORIDE; ALCOHOL; CARBOXYMETHYLCELLULOSE SODIUM, UNSPECIFIED; PROPYLENE GLYCOL; SODIUM CHLORIDE

DRUG FACTS

Analgesic Topical Gel

Active Ingredients

Asian Cobra Venom 4x

Purpose

Analgesic*

*Claim based on traditional Homeopathic practices not accepted medical evidence. Not FDA approved.

Uses:

Temporarily relieves joint pain associated with overuse and pain associated with arthritis.

Warnings:

- For external use only
- If symptoms persist or worsen, discontinue use and seek medical attention.
- Avoid contact with eyes. If product gets into eyes, flush with water. Seek medical attention.
- Not for use on open wounds.

Directions For Use:

- Remove protective wrapping.
- Liberally apply gel to the affected area and rub into joints.
- Use 3-4 times per day for the first week. Use as needed thereafter to relieve discomfort.
- Allow several days for drug to take maximum effect.

Other Information:

- Do not use if container seal is broken prior to opening.
- This product is intended for use in cases of recurring joint pain.
- This product is NOT intended to treat disease, it provides a temporary level of comfort, relief and a feeling of wellness.
- This product has been determined to be safe and effective for moderate to severe (Stage 3) chronic pain, as indicated by the Homeopathic Pharmacopeia of the United States.

KEEP OUT OF REACH OF CHILDREN

- Pregnant or nursing women and children should consult a physician before use.

Inactive Ingredients:

Benzalkonium chloride, Ethanol, Methocel, Propylene glycol, Saline

Principal Display Panel - 2 oz Carton Label

Chronic Pain Relief

Nyloxin™

TOPICAL GEL ES
ROLL ON APPLICATOR

• Joint Pain
• Neck Pain
• Arthritis Pain
• Pain from Repetitive Stress

BREAKTHROUGH
Stage 3
Pain Relief

REGULAR STRENGTH

2 oz. net wt.

Made in the U.S.A.

Principal Display Panel - 2 oz Bottle Label

Chronic Pain Relief

Nyloxin™
RS

• Joint Pain
• Neck Pain
• Arthritis Pain
• Pain from Repetitive Stress

BREAKTHROUGH
Stage 3
Pain Relief

REGULAR STRENGTH
TOPICAL GEL
ROLL ON APPLICATOR

HOMEOPATHIC

2 oz. net wt.